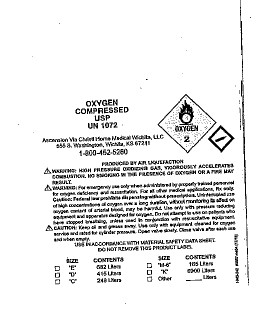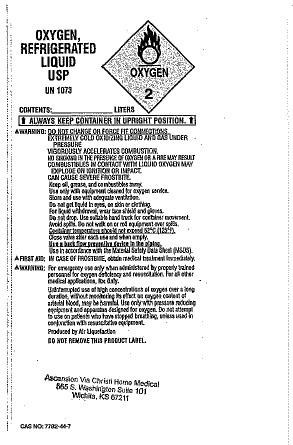 DRUG LABEL: Oxygen
NDC: 59190-416 | Form: GAS
Manufacturer: Ascension Via Christi Home Medical Wichita, LLC
Category: prescription | Type: HUMAN PRESCRIPTION DRUG LABEL
Date: 20251217

ACTIVE INGREDIENTS: OXYGEN 99 L/100 L

Oxygen, USP

Principal for Oxygen Product

OXYGEN

COMPRESSED

USP

UN 1072

Ascension Via Christi Home Medical Wichita, LLC

555 S. Washington

Wichita, KS 67211

1-800-452-5260

PRODUCED BY AIR LIQUIFICATION

WARNING: HIGH PRESSURE OXIDIZING GAS, VIGOROUSLY ACCELERATES COMBUSTION. NO SMOKING IN THE PRESENCE OF OXYGEN OR A FIRE MAY RESULT.

WARNING: For emergency use only when administered by properly trained personnel for oxygen deficiency and resuscitation. For all other medical applications, Rx only.

Caution: Federal law prohibits dispensing without prescription. Uninterrupted use of high concentrations of oxygen over a long duration, without monitoring its effect on oxygen content of arterial blood, may be harmful. Use only with pressure reducing equipment and apparatus designed for oxygen. Do not attempt to use on patients who have stopped breathing, unless used in conjuction with resuscitative equipment.

CAUTION: Keep oil and grease away. Use only with equipment cleaned for oxygen service and rated for cylinder pressure. Open valve slowly. Close valve after each use and when empty.

USE IN ACCORDANCE WITH MATERIAL SAFETY DATA SHEET.

DO NOT REMOVE THIS PRODUCT LABEL.

SIZE CONTENTS SIZE CONTENTS

__ "E" 682 Liters __ "M-6" 165 Liters

__ "D" 415 Liters __ "K" 6900 Liters

__ "C" 248 Liters __ Other ________Liters

OXYGEN,

REFRIGERATED

LIQUID USP

UN 1073

CONTENTS ________________LITERS

CAS NO: 7782-44-7

DANGER:

REFRIGERATED LIQUEFIED OXIDIZING GAS. ALWAYS

KEEP CONTAINER IN UPRIGHT POSITION. DO NOT

CHANGE OR FORCE FIT CONNECTIONS. MAY CAUSE OR INTENSIFY

FIRE; OXIDIZER, CONTAINS REFRIGERATED GAS: MAY CAUSE

CRYOGENIC BURNS OR INJURY. COMBUSTIBLES IN CONTACT WITH

LIQUID OXYGEN MAY EXPLODE ON IGNITION OR IMPACT.

Do not get in eyes, on skin, or on clothing. Keep reduction valves free

from grease and oil. In case of fire, stop leak if safe to do so. Avoid

spills. Do not walk or roll equipment over spills. Store and use in a well

ventilated place. Use only with equipment of compatible materials

of construction and rated for cylinder pressure. Wear cold insulating

gloves/face sheild/eye protection. Protect from sunlight when ambient

temperature exceeds 52 ºC/125 ºF. Container temperature should

not exceed 52 ºC/125 ºF. Close valve after each use and when

empty. Use a back flow preventative device in the piping. Do not

handle until all safety precautions have been read and understood.

Use only with equipment cleaned for oxygen service. Keep/store away

from combustible materials. Do not drop. Use suitable hand truck for

container movement.

FIRST AID:

IN CASE OF FROSTBITE: Thaw frosted parts with lukewarm water.

Do not rub affected area. Get immediate medical advice/attention.

DO NOT REMOVE THIS PRODUCT LABEL.

For emergency use only when administered by properly trained

personnel for oxygen deficiency and resuscitation. For all other medical

applications, Rx only. Uninterrupted use of high concentrations of

oxygen over a long duration, without monitoring its effect on oxygen

content of arterial blood, may be harmful. Use only with pressure

reducing equipment and apparatus designed for oxygen. Do not

attempt to use on patients who have stopped breathing unless used in

conjunction with resuscitative equipment. Produced by Air Liquefaction.

ALWAYS KEEP CONTAINER IN UPRIGHT POSITION